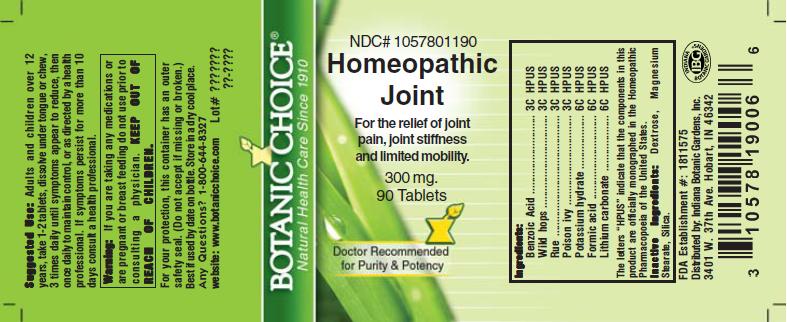 DRUG LABEL: Homeopathic Joint Formula
NDC: 10578-011 | Form: TABLET
Manufacturer: Indiana Botanic Gardens
Category: homeopathic | Type: HUMAN OTC DRUG LABEL
Date: 20110325

ACTIVE INGREDIENTS: BENZOIC ACID 3 [hp_C]/1 1; BRYONIA ALBA ROOT 3 [hp_C]/1 1; RUTA GRAVEOLENS FLOWERING TOP 3 [hp_C]/1 1; CAUSTICUM 6 [hp_C]/1 1; FORMIC ACID 6 [hp_C]/1 1; LITHIUM CARBONATE 6 [hp_C]/1 1; TOXICODENDRON PUBESCENS LEAF 3 [hp_C]/1 1
INACTIVE INGREDIENTS: DEXTROSE; MAGNESIUM STEARATE ; SILICON DIOXIDE 

Homeopathic Joint Formula

ACTIVE INGREDIENT

I n g r e d i e n t s :

Benzoic acid............................. 3C HPUS
Wild hops.............................. 3C HPUS
Rue........................ 3C HPUS
Poison ivy................... 3C HPUS
Potassium hydrate................................ 6C HPUS
Formic acid............................... 6C HPUS
Lithium carbonate..................... 6C HPUS

The letters “HPUS” indicate that the components in
this product are officially monographed in the
Homeopathic Pharmacopoeia of the United States.

PURPOSE

For the relief of joint pain, joint stiffness and limited mobility

KEEP OUT OF
REACH OF CHILDREN.

INDICATIONS AND USAGE

For the relief of joint pain, joint stiffness and limited mobility

WARNINGS

Warning: If you are taking any medications or
are pregnant or breast feeding do not use prior to
consulting a physician.

DOSAGE AND ADMINISTRATION

Suggested Use: Adults and children over 12
years, take 1-2 tablets, dissolve under tongue or
chew 3 times daily until symptoms appear to reduce,
then once daily to maintain control, or as directed by a health care
professional. If symptoms persist for more than 10 days consult a
health professional.

Inactive Ingredients: Dextrose, Magnesium
Stearate, Silica.

PACKAGE LABEL

NDC# 1057801190

Homeopathic Joint Formula

For the relief of joint pain, joint stiffness and limited mobility

300 mg.
90 Tablets

USER SAFETY WARNINGS

For your protection, this container has an outer
safety seal. (Do not accept if missing or broken.)
Best if used by date on bottle. Store in a dry cool place.
Any Questions? 1-800-644-8327
website: www.botanicchoice.com

FDA Establishment #: 1811575

Distributed by: Indiana Botanic Gardens, Inc.
3401 W. 37th Ave. Hobart, IN 46342